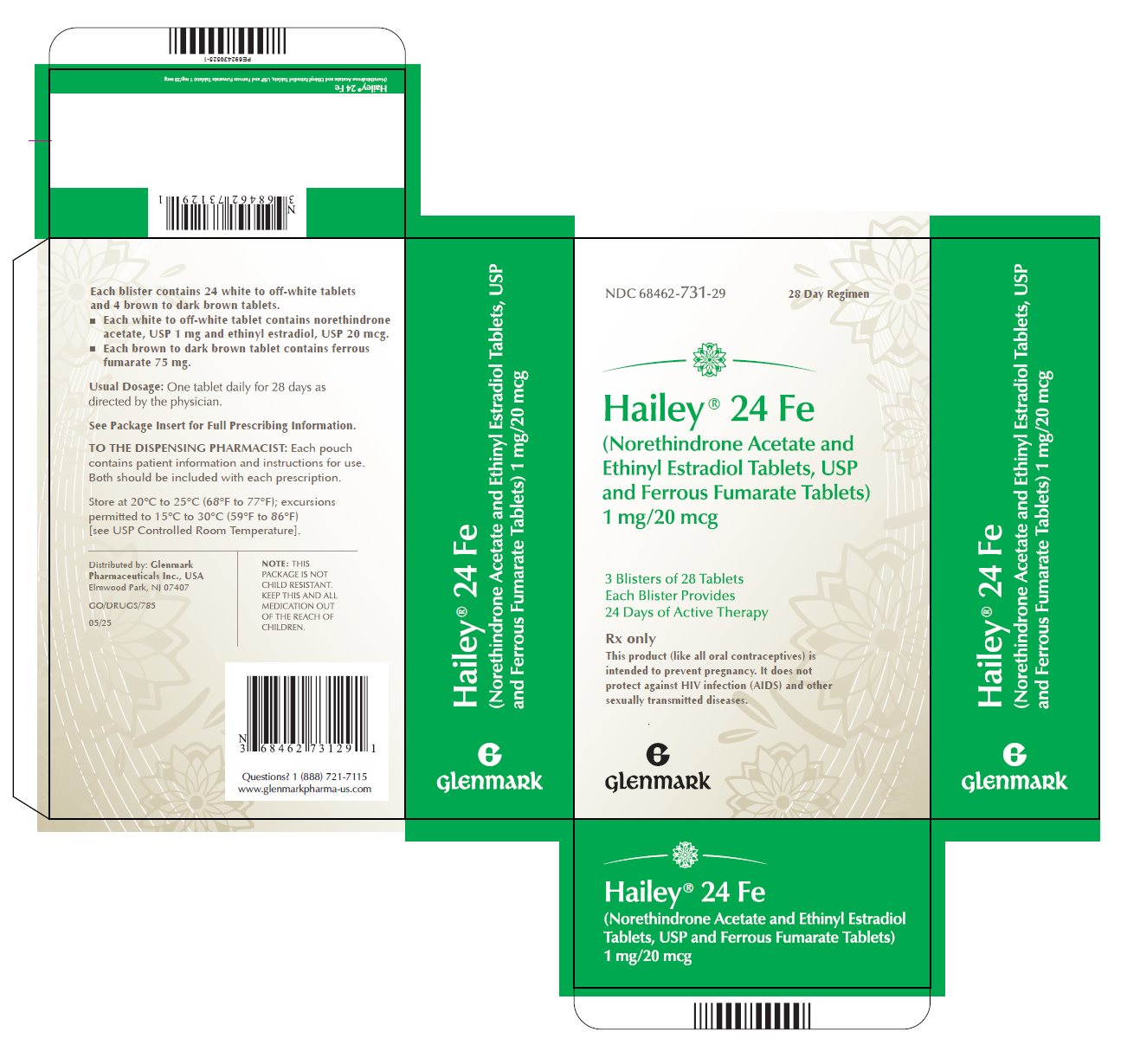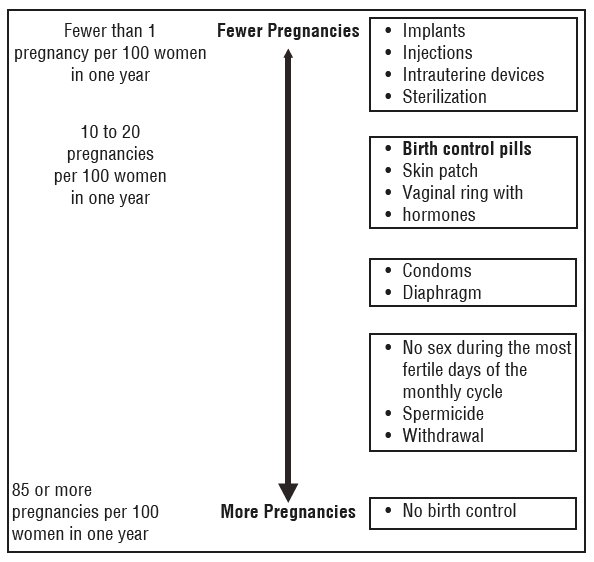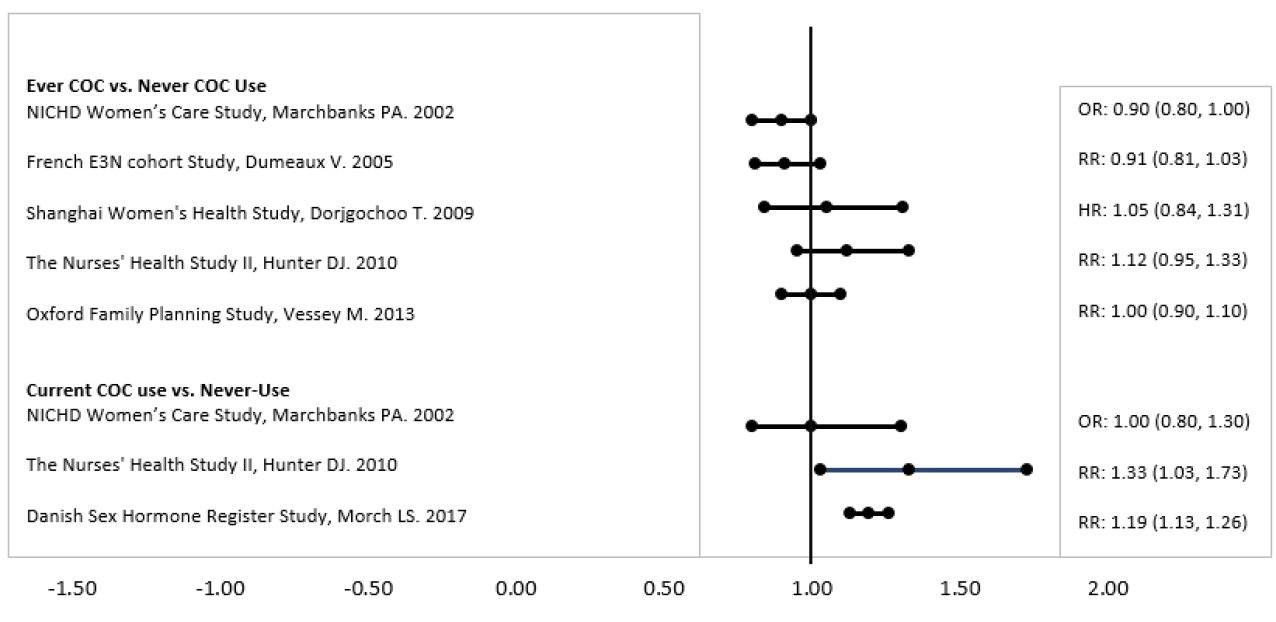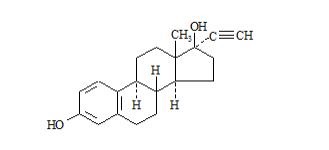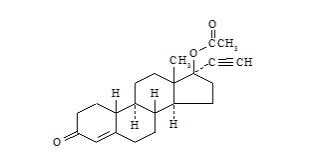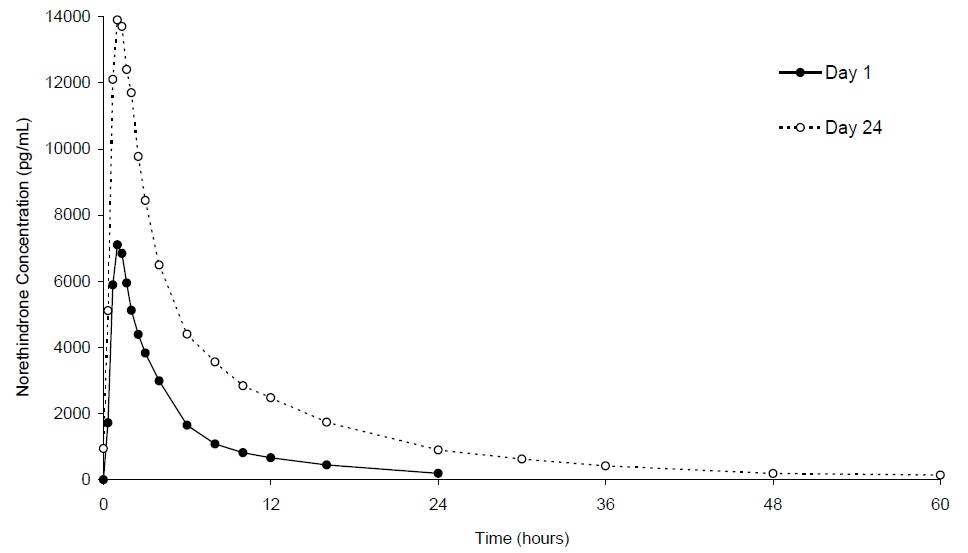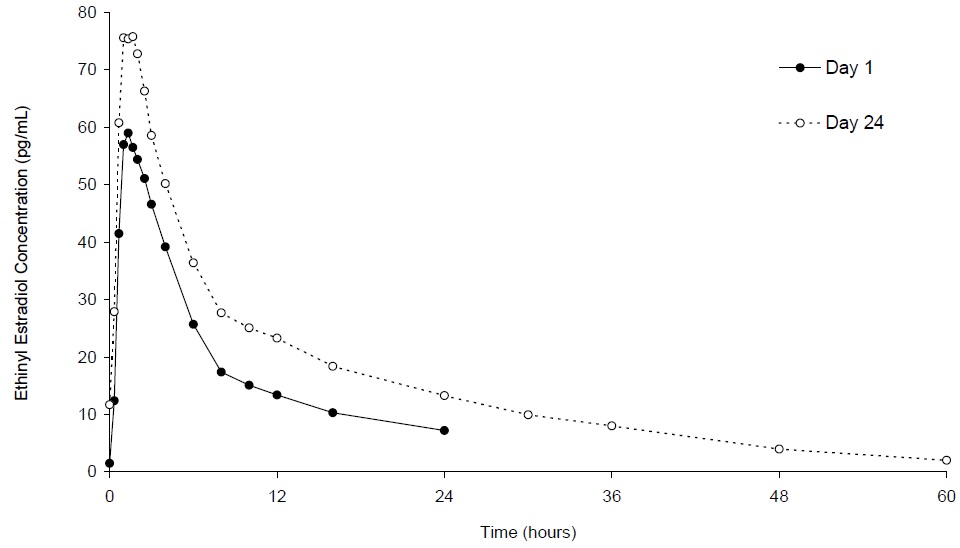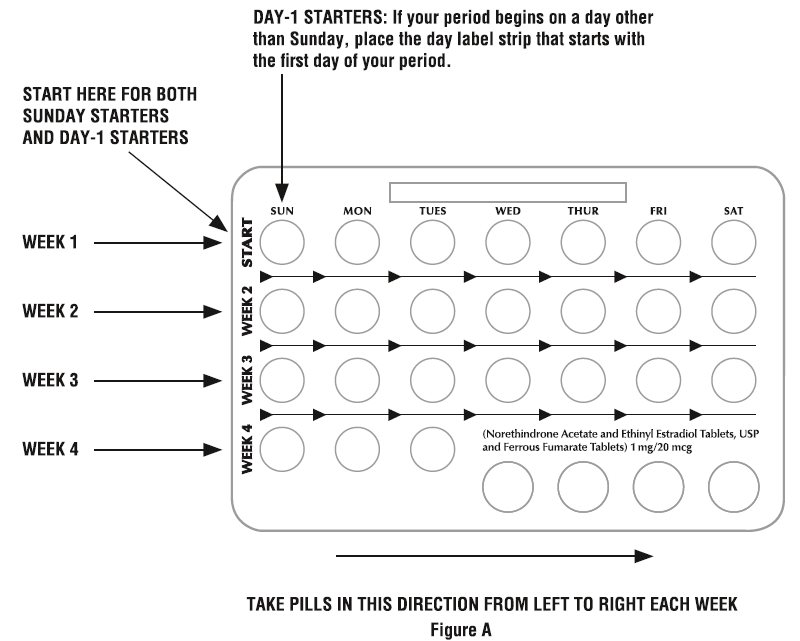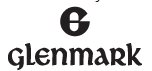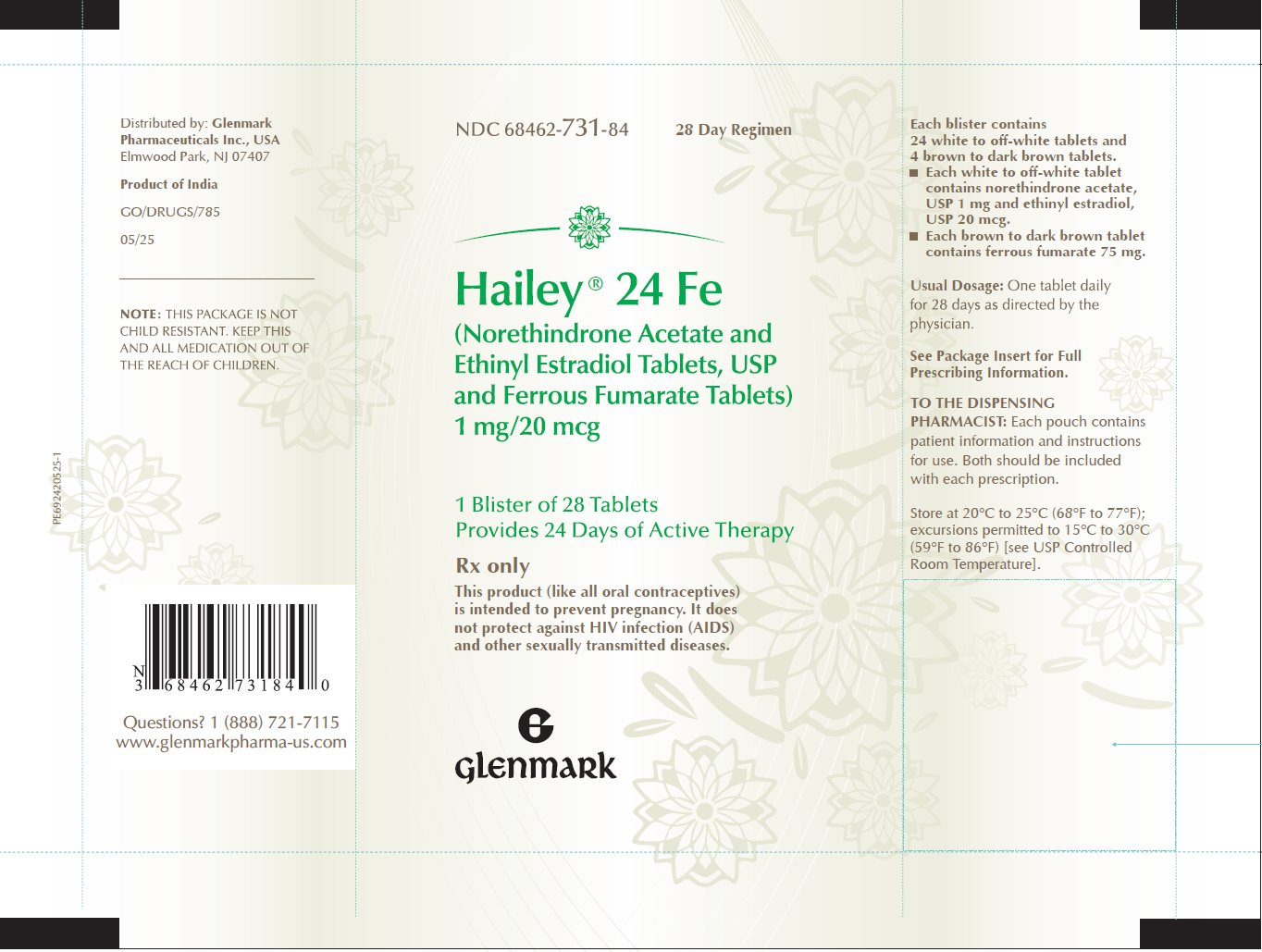 DRUG LABEL: Hailey 24 Fe
NDC: 68462-731 | Form: KIT | Route: ORAL
Manufacturer: Glenmark Pharmaceuticals Inc., USA
Category: prescription | Type: HUMAN PRESCRIPTION DRUG LABEL
Date: 20260130

ACTIVE INGREDIENTS: NORETHINDRONE ACETATE 1 mg/1 1; ETHINYL ESTRADIOL 0.02 mg/1 1
INACTIVE INGREDIENTS: ACACIA; LACTOSE MONOHYDRATE; MAGNESIUM STEARATE; STARCH, CORN; TALC; SUCROSE; FERROUS FUMARATE 75 mg/1 1; MICROCRYSTALLINE CELLULOSE; MAGNESIUM STEARATE; POVIDONE K30; SODIUM STARCH GLYCOLATE TYPE A POTATO; STARCH, CORN; TALC

HIGHLIGHTS OF PRESCRIBING INFORMATION

These highlights do not include all the information needed to use HAILEY 24 FE safely and effectively. See Full Prescribing Information for HAILEY 24 FE.
HAILEY® 24 FE (norethindrone acetate and ethinyl estradiol tablets and ferrous fumarate tablets), for oral use
Initial U.S. Approval: 1968

WARNING: CIGARETTE SMOKING AND SERIOUS CARDIOVASCULAR EVENTS

See Full Prescribing Information for complete boxed warning.

- Hailey 24 Fe is contraindicated in women over 35 years old who smoke. (4)
- Cigarette smoking increases the risk of serious cardiovascular events from combination oral contraceptives (COC) use. (4)

1 INDICATIONS AND USAGE

Hailey 24 Fe is a combination of norethindrone acetate, a progestin, and ethinyl estradiol, an estrogen, indicated for use by women to prevent pregnancy. (1) The efficacy of Hailey 24 Fe in women with a body mass index (BMI) of >35 kg/m^2 has not been evaluated. (1, 8.8)

2 DOSAGE AND ADMINISTRATION

- Take one tablet by mouth at the same time every day for 28 days (2.1)
- Take tablets in the order directed on the blister pack (2.1)
- Hailey 24 Fe may be administered without regard to meals (12.3)

3 DOSAGE FORMS AND STRENGTHS

Hailey® 24 Fe (norethindrone acetate and ethinyl estradiol tablets, USP and ferrous fumarate tablets, USP) consists of 28 tablets in the following order (3):

- 24 white to off-white tablets (active), each containing 1 mg norethindrone acetate, USP and 20 mcg ethinyl estradiol, USP.
- 4 brown to dark brown tablets (non-hormonal placebo), each containing 75 mg ferrous fumarate, USP. The ferrous fumarate tablets do not serve any therapeutic purpose.

4 CONTRAINDICATIONS

A high risk of arterial or venous thrombotic diseases (4)

- Liver tumors or liver disease (4)
- Undiagnosed abnormal uterine bleeding (4)
- Breast cancer (4)
- Co-administration with Hepatitis C drug combinations containing ombitasvir/paritaprevir/ritonavir, with or without dasabuvir (4)

5 WARNINGS AND PRECAUTIONS

- Thrombotic Disorders and Other Vascular Problems: Stop Hailey 24 Fe if a thrombotic event occurs. Stop at least 4 weeks before through 2 weeks after major surgery. Start no earlier than 4 weeks after delivery, in women who are not breastfeeding. (5.1)
- Liver disease: Discontinue Hailey 24 Fe if jaundice occurs. (5.2)
- High blood pressure: If used in women with well-controlled hypertension, monitor blood pressure and stop Hailey 24 Fe if blood pressure rises significantly. (5.4)
- Carbohydrate and lipid metabolic effects: Monitor prediabetic and diabetic women taking Hailey 24 Fe. Consider an alternative contraceptive method for women with uncontrolled dyslipidemia. (5.6)
- Headache: Evaluate significant change in headaches and discontinue Hailey 24 Fe if indicated. (5.7)
- Bleeding Irregularities and Amenorrhea: Evaluate irregular bleeding or amenorrhea. (5.8)

6 ADVERSE REACTIONS

- The most common adverse reactions (≥ 2%) were: headache, vaginal candidiasis, nausea, menstrual cramps, breast tenderness, mood changes, bacterial vaginitis, acne, and weight gain. (6.1)

To report SUSPECTED ADVERSE REACTIONS, contact Glenmark Pharmaceuticals Inc., USA at 1 (888) 721-7115 or FDA at 1-800-FDA-1088 or www.fda.gov/medwatch.

7 DRUG INTERACTIONS

- Drugs or herbal products that induce certain enzymes (for example CYP3A4) may decrease the effectiveness of COCs or increase breakthrough bleeding. Counsel patients to use a back-up method or alternative method of contraception when enzyme inducers are used with COCs. (7.1)

8 USE IN SPECIFIC POPULATIONS

- Lactation: Advise use of another contraceptive method. Hailey 24 Fe can decrease milk production. (8.2)

FULL PRESCRIBING INFORMATION

WARNING: CIGARETTE SMOKING AND SERIOUS CARDIOVASCULAR EVENTS

Cigarette smoking increases the risk of serious cardiovascular events from combination oral contraceptive (COC) use. This risk increases with age, particularly in women over 35 years of age, and with the number of cigarettes smoked. For this reason, COCs should not be used by women who are over 35 years of age and smoke [see Contraindications (4)].

1 INDICATIONS AND USAGE

Hailey 24 Fe is indicated for use by women to prevent pregnancy [see Clinical Studies (14)].

The efficacy of Hailey 24 Fe in women with a body mass index (BMI) of > 35 kg/m^2 has not been evaluated.

2 DOSAGE AND ADMINISTRATION

2.1 How to Start Hailey 24 Fe

Hailey 24 Fe is dispensed in a blister [see How Supplied/Storage and Handling (16)]. Hailey 24 Fe may be started using either a Day 1 start or a Sunday start (see Table 1). For the first cycle of a Sunday Start regimen, an additional method of contraception must be used until after the first 7 consecutive days of administration.

2.2 How to Take Hailey 24 Fe

Table 1: Instructions for Administration of Hailey 24 Fe

Starting COCs in women not currently using hormonal contraception (Day 1 Start or Sunday Start); Important:; Consider the possibility of ovulation and conception prior to initiation of this product.; Tablet Color:; - Hailey 24 Fe active tablets are white to off-white (Day 1 to Day 24). - Hailey 24 Fe inactive tablets are brown to dark brown (Day 25 to Day 28). | Day 1 Start:; - Take first white to off-white active tablet without regard to meals on the first day of menses. - Take subsequent active tablets once daily at the same time each day for a total of 24 days. - Take one brown to dark brown inactive tablet daily for 4 days and at the same time of day that active tablets were taken. - Begin each subsequent pack on the same day of the week as the first cycle pack (i.e., on the day after taking the last inactive tablet).
Starting COCs in women not currently using hormonal contraception (Day 1 Start or Sunday Start); Important:; Consider the possibility of ovulation and conception prior to initiation of this product.; Tablet Color:; - Hailey 24 Fe active tablets are white to off-white (Day 1 to Day 24). - Hailey 24 Fe inactive tablets are brown to dark brown (Day 25 to Day 28). | Sunday Start:; For each 28-day course, take in the following order:; - Take the white to off-white active tablet without regard to meals on the first Sunday after the onset of menses. Due to the potential risk of becoming pregnant, use additional non-hormonal contraception (such as condoms and spermicide) for the first 7 days of the patient’s first cycle pack of Hailey 24 Fe. - Take subsequent active tablets once daily at the same time each day for a total of 24 days. - Take one brown to dark brown tablet (ferrous fumarate) daily for the following 4 days and at the same time of day that active tablets were taken. A scheduled period should occur during the 4 days that the brown to dark brown tablets are taken. - Begin each subsequent pack on the same day of the week as the first cycle pack (i.e., on the Sunday after taking the last inactive tablet) and additional non-hormonal contraceptive is not needed.
Switching to Hailey 24 Fe from another oral contraceptive | Start on the same day that a new pack of the previous oral contraceptive would have started.
Switching from another contraceptive method to Hailey 24 Fe | Start Hailey 24 Fe:
- Transdermal patch | - On the day when next application would have been scheduled.
- Vaginal ring | - On the day when next insertion would have been scheduled
- Injection | - On the day when next injection would have been scheduled
- Intrauterine contraceptive | - On the day of removal - If the IUD is not removed on first day of the patient’s menstrual cycle, additional non-hormonal contraceptive (such as condoms and spermicide) is needed for the first seven days of the first cycle pack.
- Implant | - On the day of removal

Starting Hailey 24 Fe after Abortion or Miscarriage

First-trimester

- After a first-trimester abortion or miscarriage, Hailey 24 Fe may be started immediately. An additional method of contraception is not needed if Hailey 24 Fe is started immediately.
- If Hailey 24 Fe is not started within 5 days after termination of the pregnancy, the patient must use additional non-hormonal contraception (such as condoms and spermicide) for the first 7 days of her first 28-day course of Hailey 24 Fe.

Second-trimester

- Do not start until 4 weeks after a second-trimester abortion or miscarriage, due to the increased risk of thromboembolic disease. Start Hailey 24 Fe following the instructions in Table 1 for Sunday start. Use additional non-hormonal contraception (such as condoms and spermicide) for the first 7 days of the patient’s first 28-day course of Hailey 24 Fe [see Contraindications (4) and Warnings and Precautions (5.1)].

Starting Hailey 24 Fe after Childbirth

- Do not start until 4 weeks after delivery, due to the increased risk of thromboembolic disease. Start contraceptive therapy with Hailey 24 Fe following the instructions in Table 1 for women not currently using hormonal contraception.
- If the woman has not yet had a period postpartum, consider the possibility of ovulation and conception occurring prior to use of Hailey 24 Fe [see Contraindications (4), Warnings and Precautions (5.1), Use in Specific Populations (8.1 and 8.2)].

2.3 Missed Tablets

Table 2: Instructions for Missed Hailey 24 Fe Tablets

- If one active tablet is missed in Weeks 1, 2 or 3 | Take the tablet as soon as possible. Take the next pill at the regular time and continue taking one tablet a day until the pack is finished. Back-up contraception is not needed
- If two consecutive active tablets are missed in Week 1 or Week 2 | Take the two missed tablets as soon as possible and the next two active tablets the next day. Continue taking one tablet a day until the pack is finished. Additional non-hormonal contraception (such as condoms and spermicide) must be used as back-up if the patient has sex within 7 days after missing tablets.
- If two consecutive active tablets are missed in Week 3 or Week 4 or three or more consecutive active tablets are missed at any time | Day 1 Start: Throw out the rest of the pack and start a new pack that same day.; Sunday Start: Continue taking one tablet a day until Sunday, then throw out the rest of the pack and start a new pack that same day.; Additional non-hormonal contraception (such as condoms and spermicide) must be used as back-up if the patient has sex within 7 days after missing 3 tablets.

2.4 Advice in Case of Gastrointestinal Disturbances

In case of severe vomiting or diarrhea, absorption may not be complete and additional contraceptive measures must be taken. If vomiting or diarrhea occurs within 3 to 4 hours after taking a white to off-white tablet, handle this as a missed tablet [see Dosage and Administration (2.3)].

3 DOSAGE FORMS AND STRENGTHS

Hailey® 24 Fe (norethindrone acetate and ethinyl estradiol tablets, USP and ferrous fumarate tablets, USP) is available in blister packs.

Each blister pack (28 tablets) contains in the following order:

- 24 white to off-white, round, flat faced beveled edge, uncoated tablets debossed with ‘16’ on one side and ‘G’ on the other side and each containing 1 mg norethindrone acetate, USP and 20 mcg ethinyl estradiol, USP.
- 4 brown to dark brown, round, flat faced beveled edge, uncoated tablets debossed with ‘17’ on one side and ‘G’ on the other side and each containing 75 mg ferrous fumarate, USP. The ferrous fumarate tablets do not serve any therapeutic purpose.

4 CONTRAINDICATIONS

Hailey 24 Fe is contraindicated in females who are known to have or develop the following conditions:

- A high risk of arterial or venous thrombotic diseases. Examples include women who are known to:
- Smoke, if over age 35 [see Boxed Warning and Warnings and Precautions (5.1)]
- Have deep vein thrombosis or pulmonary embolism, now or in the past [see Warnings and Precautions (5.1)]
- Have inherited or acquired hypercoagulopathies [see Warnings and Precautions (5.1)]
- Have cerebrovascular disease [see Warnings and Precautions (5.1)]
- Have coronary artery disease [see Warnings and Precautions (5.1)]
- Have thrombogenic valvular or thrombogenic rhythm diseases of the heart (for example, subacute bacterial endocarditis with valvular disease, or atrial fibrillation) [see Warnings and Precautions (5.1)]
- Have uncontrolled hypertension [see Warnings and Precautions (5.4)]
- Have diabetes mellitus with vascular disease [see Warnings and Precautions (5.6)]
- Have headaches with focal neurological symptoms or have migraine headaches with aura [see Warnings and Precautions (5.7)]
  - Women over age 35 with any migraine headaches [see Warnings and Precautions (5.7)]
- Liver tumors, benign or malignant, or liver disease [see Warnings and Precautions (5.2)]
- Undiagnosed abnormal uterine bleeding [see Warnings and Precautions (5.8)]
● Current diagnosis of, or history of, breast cancer, which may be hormone sensitive[see Warnings and Precautions (5.11)]
● Use of Hepatitis C drug combinations containing ombitasvir/paritaprevir/ritonavir, with or without dasabuvir, due to the potential for ALT elevations [see Warnings and Precautions (5.3)]

5 WARNINGS AND PRECAUTIONS

5.1 Thrombotic Disorders and Other Vascular Problems

- Stop Hailey 24 Fe if an arterial thrombotic event or venous thromboembolic (VTE) event occurs.
- Stop Hailey 24 Fe if there is unexplained loss of vision, proptosis, diplopia, papilledema, or retinal vascular lesions. Evaluate for retinal vein thrombosis immediately [see Adverse Reactions (6.2)].
- If feasible, stop Hailey 24 Fe at least 4 weeks before and through 2 weeks after major surgery or other surgeries known to have an elevated risk of VTE as well as during the following prolonged immobilization.
- Start Hailey 24 Fe no earlier than 4 weeks after delivery, in women who are not breastfeeding. The risk of postpartum VTE decreases after the third postpartum week, whereas the risk of ovulation increases after the third postpartum week.
- The use of COCs increases the risk of VTE. However, pregnancy increases the risk of VTE as much or more than the use of COCs. The risk of VTE in women using COCs is 3 to 9 cases per 10,000 woman-years. The risk of VTE is highest during the first year of use of a COCs and when restarting oral contraception after a break of 4 weeks or longer. The risk of thromboembolic disease due to COCs gradually disappears after COC use is discontinued.
- Use of COCs also increases the risk of arterial thromboses such as strokes and myocardial infarctions, especially in women with other risk factors for these events. COCs have been shown to increase both the relative and attributable risks of cerebrovascular events (thrombotic and hemorrhagic strokes). This risk increases with age, particularly in women over 35 years of age who smoke.
- Use COCs with caution in women with cardiovascular disease risk factors.

5.2 Liver Disease

Impaired Liver Function

Do not use Hailey 24 Fe in women with liver disease, such as acute viral hepatitis or severe (decompensated) cirrhosis of liver [see Contraindications (4)]. Acute or chronic disturbances of liver function may necessitate the discontinuation of COC use until markers of liver function return to normal and COC causation has been excluded. Discontinue Hailey 24 Fe if jaundice develops.

Liver Tumors

Hailey 24 Fe is contraindicated in women with benign and malignant liver tumors [see Contraindications (4)]. Hepatic adenomas are associated with COC use. An estimate of the attributable risk is 3.3 cases per 100,000 COC users. Rupture of hepatic adenomas may cause death through intra-abdominal hemorrhage.

Studies have shown an increased risk of developing hepatocellular carcinoma in long-term (>8 years) COC users. However, the risk of liver cancers in COC users is less than one case per million users.

5.3 Risk of Liver Enzyme Elevations with Concomitant Hepatitis C Treatment

During clinical trials with the Hepatitis C combination drug regimen that contains ombitasvir/paritaprevir/ritonavir, with or without dasabuvir, ALT elevations greater than 5 times the upper limit of normal (ULN), including some cases greater than 20 times the ULN, were significantly more frequent in women using ethinyl estradiol-containing medications, such as COCs. Discontinue Hailey 24 Fe prior to starting therapy with the combination drug regimen ombitasvir/paritaprevir/ritonavir, with or without dasabuvir [see Contraindications (4)]. Hailey 24 Fe can be restarted approximately 2 weeks following completion of treatment with the Hepatitis C combination drug regimen.

5.4 High Blood Pressure

Hailey 24 Fe is contraindicated in women with uncontrolled hypertension or hypertension with vascular disease [see Contraindications (4)]. For women with well-controlled hypertension, monitor blood pressure and stop Hailey 24 Fe if blood pressure rises significantly.

An increase in blood pressure has been reported in women taking COCs, and this increase is more likely in older women with extended duration of use. The incidence of hypertension increases with increasing concentrations of progestin.

5.5 Gallbladder Disease

Studies suggest a small increased relative risk of developing gallbladder disease among COC users. Use of COCs may worsen existing gallbladder disease. A past history of COC-related cholestasis predicts an increased risk with subsequent COC use. Women with a history of pregnancy-related cholestasis may be at an increased risk for COC related cholestasis.

5.6 Carbohydrate and Lipid Metabolic Effects

Carefully monitor prediabetic and diabetic women who are taking Hailey 24 Fe. COCs may decrease glucose tolerance.

Consider alternative contraception for women with uncontrolled dyslipidemias. A small proportion of women will have adverse lipid changes while on COCs.

Women with hypertriglyceridemia, or a family history thereof, may be at an increased risk of pancreatitis when using COCs.

5.7 Headache

If a woman taking Hailey 24 Fe develops new headaches that are recurrent, persistent, or severe, evaluate the cause and discontinue Hailey 24 Fe if indicated. Consider discontinuation of Hailey 24 Fe in the case of increased frequency or severity of migraine during COC use (which may be prodromal of a cerebrovascular event).

5.8 Bleeding Irregularities and Amenorrhea

Unscheduled Bleeding and Spotting

Unscheduled (breakthrough or intracyclic) bleeding and spotting sometimes occur in patients on COCs, especially during the first three months of use. If bleeding persists or occurs after previously regular cycles, check for causes such as pregnancy or malignancy. If pathology and pregnancy are excluded, bleeding irregularities may resolve over time or with a change to a different contraceptive product.

In a clinical trial of norethindrone acetate and ethinyl estradiol tablets and ferrous fumarate tablets, the frequency and duration of unscheduled bleeding and/or spotting was assessed in 743 women (3,823 28-day cycles). A total of 10 subjects (1.3%) discontinued norethindrone acetate and ethinyl estradiol tablets and ferrous fumarate tablets, at least in part, due to bleeding or spotting. Based on data from the clinical trial, [24 to 38%] of women using norethindrone acetate and ethinyl estradiol tablets and ferrous fumarate tablets experienced unscheduled bleeding per cycle in the six months of the trial. The percent of women who experienced unscheduled bleeding tended to decrease over time.

Amenorrhea and Oligomenorrhea

Women who use norethindrone acetate and ethinyl estradiol tablets and ferrous fumarate tablets may experience absence of withdrawal bleeding, even if they are not pregnant. In the clinical trial with norethindrone acetate and ethinyl estradiol tablets and ferrous fumarate tablets, 31 to 41% of the women using norethindrone acetate and ethinyl estradiol tablets and ferrous fumarate tablets did not have a withdrawal menses in at least one of 6 cycles of use.

Some women may experience amenorrhea or oligomenorrhea after discontinuation of COCs, especially when such a condition was preexistent.

If scheduled (withdrawal) bleeding does not occur, consider the possibility of pregnancy. If the patient has not adhered to the prescribed dosing schedule (missed one or more active tablets or started taking them on a day later than she should have), consider the possibility of pregnancy at the time of the first missed period and take appropriate diagnostic measures. If the patient has adhered to the prescribed regimen and misses two consecutive periods, rule out pregnancy.

5.9 COC Use Before or During Early Pregnancy

Extensive epidemiologic studies have revealed no increased risk of birth defects in women who have used oral contraceptives prior to pregnancy. Studies also do not suggest a teratogenic effect, particularly in so far as cardiac anomalies and limb reduction defects are concerned, when oral contraceptives are taken inadvertently during early pregnancy. Discontinue Hailey 24 Fe use if pregnancy is confirmed.

Administration of COCs to induce withdrawal bleeding should not be used as a test for pregnancy [see Use in Specific Populations (8.1)].

5.10 Depression

Carefully observe women with a history of depression and discontinue Hailey 24 Fe if depression recurs to a serious degree.

5.11 Malignant Neoplasms

Breast Cancer

Hailey 24 Fe is contraindicated in women who currently have or have had breast cancer because breast cancer may be hormonally-sensitive [see Contraindications (4)].

Epidemiology studies have not found a consistent association between use of combined oral contraceptives (COCs) and breast cancer risk. Studies do not show an association between ever (current or past) use of COCs and risk of breast cancer. However, some studies report a small increase in the risk of breast cancer among current or recent users (<6 months since last use) and current users with longer duration of COCuse [see Postmarketing Experience (6.2)].

Cervical Cancer

Some studies suggest that COCs are associated with an increase in the risk of cervical cancer or intraepithelial neoplasia. However, there is controversy about the extent to which these findings may be due to differences in sexual behavior and other factors.

5.12 Effect on Binding Globulins

The estrogen component of COCs may raise the serum concentrations of thyroxine-binding globulin, sex hormone-binding globulin, and cortisol-binding globulin. The dose of replacement thyroid hormone or cortisol therapy may need to be increased.

5.13 Monitoring

A woman who is taking COCs should have a yearly visit with her healthcare provider for a blood pressure check and for other indicated healthcare.

5.14 Hereditary Angioedema

In women with hereditary angioedema, exogenous estrogens may induce or exacerbate symptoms of angioedema.

5.15 Chloasma

Chloasma may occasionally occur, especially in women with a history of chloasma gravidarum. Women with a tendency to chloasma should avoid exposure to the sun or ultraviolet radiation while taking Hailey 24 Fe.

6 ADVERSE REACTIONS

The following serious adverse reactions with the use of COCs are discussed elsewhere in the labeling:

- Serious cardiovascular events and stroke [see Boxed Warning and Warnings and Precautions (5.1)]
- Vascular events [see Warnings and Precautions (5.1)]
- Liver disease [see Warnings and Precautions (5.2)]

Adverse reactions commonly reported by COC users are:

- Irregular uterine bleeding
- Nausea
- Breast tenderness
- Headache

6.1 Clinical Trial Experience

Because clinical trials are conducted under widely varying conditions, adverse reaction rates observed in the clinical trials of a drug cannot be directly compared to the rates in the clinical trials of another drug and may not reflect the rates observed in practice.

The safety of norethindrone acetate and ethinyl estradiol tablets and ferrous fumarate tablets were evaluated in 743 subjects who participated in an open-label, randomized, active-controlled, multicenter clinical trial of norethindrone acetate and ethinyl estradiol tablets and ferrous fumarate tablets for contraception. This trial examined healthy, non-pregnant volunteers aged 18 to 45 years, who were sexually active and had a body mass index of ≤ 35 kg/m^2. Subjects were followed for up to six 28-day cycles providing a total of 3,823 treatment-cycles of exposure.

Common Adverse Reactions (≥ 2% of all subjects): The most common adverse reactions reported by at least 2% of the 743 women using norethindrone acetate and ethinyl estradiol tablets and ferrous fumarate tablets were the following, in order of decreasing incidence: headache (6.3%), vaginal candidiasis (6.1%), nausea (4.6%), menstrual cramps (4.4%), breast tenderness (3.4%), mood changes (including mood swings (2.2%) and depression (1.1%), bacterial vaginitis (3.1%), acne (2.7%), and weight gain (2.0%).

Adverse Reactions Leading to Study Discontinuation: Among the 743 women using norethindrone acetate and ethinyl estradiol tablets and ferrous fumarate tablets, 46 women (6.2%) withdrew because of an adverse event. Adverse events occurring in 3 or more subjects leading to discontinuation of treatment were, in decreasing order: abnormal bleeding (0.9%), nausea (0.8%), mood changes (0.8%), menstrual cramps (0.4%), increased blood pressure (0.4%), and irregular bleeding (0.4%).

6.2 Postmarketing Experience

Five studies that compared breast cancer risk between ever-users (current or past use) of COCs and never-users of COCs reported no association between ever use of COCs and breast cancer risk, with effect estimates ranging from 0.90 to 1.12 (Figure 1).

Three studies compared breast cancer risk between current or recent COC users (<6 months since last use) and never users of COCs (Figure 1). One of these studies reported no association between breast cancer risk and COC use. The other two studies found an increased relative risk of 1.19 to 1.33 with current or recent use. Both of these studies found an increased risk of breast cancer with current use of longer duration, with relative risks ranging from 1.03 with less than one year of COC use to approximately 1.4 with more than 8 to 10 years of COC use.

Figure 1. Relevant Studies of Risk of Breast Cancer with Combined Oral Contraceptives

RR = relative risk; OR = odds ratio; HR = hazard ratio. “ever COC” are females with current or past COC use; “never COC use” are females that never used COCs.

The following adverse reactions have been identified during post approval use of norethindrone acetate and ethinyl estradiol tablets and ferrous fumarate tablets. Because these reactions are reported voluntarily from a population of uncertain size, it is difficult to reliably estimate their frequency or evaluate a causal relationship to drug exposure.

Cardiovascular: chest pain, palpitations, tachycardia, angina pectoris, myocardial infarction.

Endocrine disorders: hypothyroidism, hyperthyroidism.

Eye disorders: blurred vision, visual impairment, transient blindness, corneal thinning, change in corneal curvature (steepening).

GI disorders: nausea, vomiting, abdominal pain, constipation, pancreatitis.

Hepatobiliary disorders: cholelithiasis, cholecystitis, hepatic adenoma, hemangioma of liver.

Immune system disorders: anaphylactic reactions, including urticaria, angioedema, and severe reactions with respiratory and circulatory symptoms.

Infections: vaginal infection.

Metabolism and nutrition disorders: change in weight or appetite (increase or decrease).

hypoglycemia, diabetes mellitus, anemia.

Musculoskeletal and connective tissue disorders: myalgia.

Skin and subcutaneous disorders: alopecia, rash (generalized and allergic), pruritus, skin discoloration, night sweats, swelling face or lips, hirsutism, skin burning sensation, erythema multiforme, erythema nodosum, hemorrhagic eruption.

Nervous system disorders: headache, dizziness, migraine, hyperesthesia, paraesthesia, hypoaesthesia, somnolence, loss of consciousness, sensory disturbance.

Psychiatric disorders: mood swings, depression, insomnia, anxiety, suicidal ideation, panic attack, changes in libido, bipolar disorder, dissociation, homicidal ideation.

Renal and urinary disorders: pollakiuria, dysuria, cystitis-like syndrome.

Reproductive system and breast disorders: breast changes (tenderness, pain, enlargement, and secretion), premenstrual syndrome, ovarian cyst, pelvic pain, ovarian cyst ruptured, pelvic fluid collection.

Vascular disorders: hot flush, thrombosis/embolism (coronary artery, pulmonary, cerebral, deep vein), migraine, transient ischemic attack, ischemic stroke.

7 DRUG INTERACTIONS

Consult the labeling of concurrently used drugs to obtain further information about interactions with oral contraceptives or the potential for enzyme alterations.

7.1 Effects of Other Drugs on Combined Oral Contraceptives

Substances decreasing the plasma concentrations of COCs and potentially diminishing the efficacy of COCs:

Drugs or herbal products that induce certain enzymes, including cytochrome P450 3A4 (CYP3A4), may decrease the plasma concentrations of COCs and potentially diminish the effectiveness of COCs or increase breakthrough bleeding. Some drugs or herbal products that may decrease the effectiveness of oral contraceptives including phenytoin, barbiturates, carbamazepine, bosentan, felbamate, griseofulvin, oxcarbazepine, rifampicin, topiramate, rifabutin, rufinamide, aprepitant, and products containing St. John’s wort. Interactions between COCs and other drugs may lead to breakthrough bleeding and/or contraceptive failure. Counsel women to use an alternative method of contraception or a back-up method when enzyme inducers are used with COCs, and to continue back-up contraception for 28 days after discontinuing the enzyme inducer to ensure contraceptive reliability.

Substances increasing the plasma concentrations of COCs:

Co-administration of atorvastatin or rosuvastatin and certain COCs containing ethinyl estradiol (EE) increase AUC values for EE by approximately 20 to 25%. Ascorbic acid and acetaminophen may increase plasma EE concentrations, possibly by inhibition of conjugation. CYP3A4 inhibitors such as itraconazole, voriconazole, fluconazole, grapefruit juice, or ketoconazole may increase plasma hormone concentrations.

Human immunodeficiency virus (HIV)/Hepatitis C virus (HCV) protease inhibitors and non-nucleoside reverse transcriptase inhibitors:

Significant changes (increase or decrease) in the plasma concentrations of estrogen and/or progestin have been noted in some cases of co-administration with HIV protease inhibitors (decrease [e.g., nelfinavir, ritonavir, darunavir/ritonavir, (fos)amprenavir/ritonavir, lopinavir/ritnoavir, and tipranavir/ritonavir] or increase [e.g., indinavir and atazanavir/ritonavir])/HCV protease inhibitors or with non-nucleoside reverse transcriptase inhibitors (decrease [e.g., nevirapine] or increase [e.g., etravirine]).

7.2 Effects of Combined Oral Contraceptives on Other Drugs

COCs containing EE may inhibit the metabolism of other compounds (e.g., cyclosporine, prednisolone, theophylline, tizanidine, and voriconazole) and increase their plasma concentrations. COCs have been shown to decrease plasma concentrations of acetaminophen, clofibric acid, morphine, salicylic acid, and temazepam. Significant decrease in plasma concentration of lamotrigine has been shown, likely due to induction of lamotrigine glucuronidation. This may reduce seizure control; therefore, dosage adjustments of lamotrigine may be necessary.

Women on thyroid hormone replacement therapy may need increased doses of thyroid hormone because the serum concentration of thyroid-binding globulin increases with use of COCs [see Warnings and Precautions (5.12)].

7.3 Concomitant Use with HCV Combination Therapy – Liver Enzyme Elevation

Co-administration of Hailey 24 Fe with HCV drug combinations containing ombitasvir/paritaprevir/ritonavir, with or without dasabuvir is contraindicated due to potential for ALT elevations [see Warnings and Precautions (5.3)]. Co-administration of Hailey 24 Fe and glecaprevir/pibrentasvir is not recommended due to potential for ALT elevations.

7.4 Interactions with Laboratory Tests

The use of contraceptive steroids may influence the results of certain laboratory tests, such as coagulation factors, lipids, glucose tolerance, and binding proteins.

8 USE IN SPECIFIC POPULATIONS

8.1 Pregnancy

Risk Summary

There is no use for contraception in pregnancy; therefore, Hailey 24 Fe should be discontinued during pregnancy. Epidemiologic studies and meta-analyses have not found an increased risk of genital or nongenital birth defects (including cardiac anomalies and limb-reduction defects) following exposure to CHCs before conception or during early pregnancy.

In the U.S. general population, the estimated background risk of major birth defects and miscarriage in clinically recognized pregnancies is 2 to 4 percent and 15 to 20 percent, respectively.

Data

Human Data

Epidemiologic studies and meta-analyses have not found an increased risk of genital or nongenital birth defects (including cardiac anomalies and limb-reduction defects) following exposure to CHCs before conception or during early pregnancy.

8.2 Lactation

Risk Summary

Contraceptive hormones and/or metabolites are present in human milk. CHCs can reduce milk production in breastfeeding females. This reduction can occur at any time but is less likely to occur once breastfeeding is well-established. When possible, advise the nursing female to use other methods of contraception until she discontinues breastfeeding [see Dosage and Administration (2.2).] The developmental and health benefits of breastfeeding should be considered along with the mother’s clinical need for Hailey 24 Fe and any potential adverse effects on the breastfed child from Hailey 24 Fe or from the underlying maternal condition.

8.4 Pediatric Use

Safety and efficacy of norethindrone acetate and ethinyl estradiol tablets and ferrous fumarate tablets have been established in women of reproductive age. Efficacy is expected to be the same in postpubertal adolescents under the age of 18 years as for users 18 years and older. Use of this product before menarche is not indicated.

8.5 Geriatric Use

Norethindrone acetate and ethinyl estradiol tablets and ferrous fumarate tablets have not been studied in postmenopausal women and is not indicated in this population.

8.6 Hepatic Impairment

The pharmacokinetics of norethindrone acetate and ethinyl estradiol tablets and ferrous fumarate tablets have not been studied in subjects with hepatic impairment. However, steroid hormones may be poorly metabolized in patients with hepatic impairment. Acute or chronic disturbances of liver function may necessitate the discontinuation of COC use until markers of liver function return to normal and COC causation has been excluded [see Contraindications (4) and Warnings and Precautions (5.2)].

8.7 Renal Impairment

The pharmacokinetics of norethindrone acetate and ethinyl estradiol tablets and ferrous fumarate tablets have not been studied in women with renal impairment.

8.8 Body Mass Index

The safety and efficacy of norethindrone acetate and ethinyl estradiol tablets and ferrous fumarate tablets in women with a body mass index (BMI) > 35 kg/m^2 has not been evaluated [see Clinical Studies (14)].

10 OVERDOSAGE

There have been no reports of serious ill effects from overdose of oral contraceptives, including ingestion by children. Overdosage may cause withdrawal bleeding in females and nausea.

11 DESCRIPTION

Hailey® 24 Fe (norethindrone acetate and ethinyl estradiol tablets, USP and ferrous fumarate tablets, USP) is a combination oral contraceptive for oral administration consisting of active tablets containing norethindrone acetate, USP, a progestin, and ethinyl estradiol, USP, an estrogen, and placebo tablets containing ferrous fumarate, USP which serve no therapeutic purpose.

- Each active white to off-white tablet contains 1 mg norethindrone acetate, USP and 20 mcg ethinyl estradiol, USP. Inactive ingredients include acacia, corn starch, lactose monohydrate, magnesium stearate, sucrose and talc.
- Each placebo brown to dark brown tablet contains 75 mg ferrous fumarate, microcrystalline cellulose, magnesium stearate, povidone, sodium starch glycolate, corn starch and talc. The ferrous fumarate tablets do not serve any therapeutic purpose.

The chemical name of ethinyl estradiol, USP is [19-Norpregna-1,3,5(10)-trien-20-yne-3,17-diol, (17α)-]. The empirical formula of ethinyl estradiol, USP is C20H24O2 and the structural formula is:

The chemical name of norethindrone acetate, USP is [19-Norpregn-4-en-20-yn-3-one, 17-(acetyloxy)-, (17α)-]. The empirical formula of norethindrone acetate, USP is C22H28O3 and the structural formula is:

12 CLINICAL PHARMACOLOGY

12.1 Mechanism of Action

CHCs prevent pregnancy primarily by suppressing ovulation.

12.2 Pharmacodynamics

No specific pharmacodynamic studies were conducted with norethindrone acetate and ethinyl estradiol tablets and ferrous fumarate tablets.

12.3 Pharmacokinetics

Absorption

Norethindrone acetate appears to be completely and rapidly deacetylated to norethindrone after oral administration, because the disposition of norethindrone acetate is indistinguishable from that of orally administered norethindrone. Norethindrone acetate and ethinyl estradiol are rapidly absorbed from norethindrone acetate and ethinyl estradiol tablets and ferrous fumarate tablets, with maximum plasma concentrations of norethindrone and ethinyl estradiol occurring 1 to 4 hours postdose. Both are subject to first-pass metabolism after oral dosing, resulting in an absolute bioavailability of approximately 64% for norethindrone and 43% for ethinyl estradiol.

The plasma norethindrone and ethinyl estradiol pharmacokinetics following single- and multiple-dose administrations of norethindrone acetate and ethinyl estradiol tablets and ferrous fumarate tablets in 17 healthy female volunteers are provided in Figures 2 and 3, and Table 3.

Following multiple-dose administration of norethindrone acetate and ethinyl estradiol tablets and ferrous fumarate tablets, mean maximum concentrations of norethindrone and ethinyl estradiol were increased by 95% and 27%, respectively, as compared to single-dose administration. Mean norethindrone and ethinyl estradiol exposures (AUC values) were increased by 164% and 51% respectively, as compared to single-dose administration of norethindrone acetate and ethinyl estradiol tablets and ferrous fumarate tablets.

Steady-state with respect to norethindrone was reached by Day 17 and steady-state with respect to ethinyl estradiol was reached by Day 13.

Mean SHBG concentrations were increased by 150% from baseline (57.5 nmol/L) to 144 nmol/L at steady-state.

Figure 2. Mean Plasma Norethindrone Concentration-Time Profiles Following Single- and Multiple-Dose Oral Administration of Norethindrone Acetate and Ethinyl Estradiol Tablets and Ferrous Fumarate Tablets to Healthy Female Volunteers Under Fasting Condition (n = 17)

Figure 3. Mean Plasma Ethinyl Estradiol Concentration-Time Profiles Following Single- and Multiple-Dose Oral Administration of Norethindrone Acetate and Ethinyl Estradiol Tablets and Ferrous Fumarate Tablets to Healthy Female Volunteers Under Fasting Condition (n = 17)

Table 3. Summary of Norethindrone (NE) and Ethinyl Estradiol (EE) Pharmacokinetics Following Single- and Multiple-Dose Oral Administration of Norethindrone Acetate and Ethinyl Estradiol Tablets and Ferrous Fumarate Tablets to Healthy Female Volunteers Under Fasting Condition (n = 17)

Regimen | Analyte | Arithmetic Meana (% CV) by Pharmacokinetic Parameter
Regimen | Analyte | Cmax; (pg/mL) | tmax; (hr) | AUC(0 to 24); (pg/mL•h) | Cmin; (pg/mL) | t½; (hr) | Cavg; (pg/mL)
Day 1; (Single Dose) | NE | 8420; (31) | 1.0; (0.7 to 4.0) | 33390; (40) | -- | -- | --
Day 1; (Single Dose) | EE | 64.5; (27) | 1.3; (0.7 to 4.0) | 465.4; (26) | -- | -- | --
Day 1; (Single Dose) | SHBG | -- | -- | -- | 57.5; (37)b | -- | --
Day 24 (Multiple Dose) | NE | 16400; (26) | 1.3; (0.7 to 4.0) | 88160; (30) | 880; (51) | 8.4 | 3670; (30)
Day 24 (Multiple Dose) | EE | 81.9; (24) | 1.7; (1.0 to 2.0) | 701.3; (28) | 11.4; (43) | 14.5 | 29.2; (28)
Day 24 (Multiple Dose) | SHBG | -- | -- | -- | 144; (24) | -- | --

Cmax = Maximum plasma concentration

tmax = Time of Cmax

Cmin = minimum plasma concentration at steady-state

AUC(0 to 24) = Area under plasma concentration versus time curve from 0 to 24 hours

t½ = Apparent first-order terminal elimination half-life

Cavg = Average plasma concentration = AUC(0 to 24)/24

% CV = Coefficient of Variation (%)

SHBG = Sex Hormone Binding Globulin (nmol/L)

aThe harmonic mean (0.693/mean apparent elimination rate constant) is reported for t½, and the median (range) is reported for tmax.

bThe SHBG concentration reported here is the pre-dose concentration.

Food Effect

A single-dose administration of norethindrone acetate and ethinyl estradiol tablets and ferrous fumarate tablet with food decreased the maximum concentration of norethindrone by 11% and increased the extent of absorption by 27% and decreased the maximum concentration of ethinyl estradiol by 30% but not the extent of absorption.

Distribution

Volume of distribution of norethindrone and ethinyl estradiol ranges from 2 to 4 L/kg. Plasma protein binding of both steroids is extensive (>95%); norethindrone binds to both albumin and SHBG, whereas ethinyl estradiol binds only to albumin. Although ethinyl estradiol does not bind to SHBG, it induces SHBG synthesis.

Metabolism

Norethindrone undergoes extensive biotransformation, primarily via reduction, followed by sulfate and glucuronide conjugation. The majority of metabolites in the circulation are sulfates, with glucuronides accounting for most of the urinary metabolites.

Ethinyl estradiol is also extensively metabolized, both by oxidation and by conjugation with sulfate and glucuronide. Sulfates are the major circulating conjugates of ethinyl estradiol and glucuronides predominate in urine. The primary oxidative metabolite is 2-hydroxy ethinyl estradiol, formed by the CYP3A4 isoform of cytochrome P450. Part of the first-pass metabolism of ethinyl estradiol is believed to occur in gastrointestinal mucosa. Ethinyl estradiol may undergo enterohepatic circulation.

Excretion

Norethindrone and ethinyl estradiol are excreted in both urine and feces, primarily as metabolites. Plasma clearance values for norethindrone and ethinyl estradiol are similar (approximately 0.4 L/hr/kg). Steady-state elimination half-lives of norethindrone and ethinyl estradiol following administration of norethindrone acetate and ethinyl estradiol tablets and ferrous fumarate tablets are approximately 8 hours and 14 hours, respectively.

13 NONCLINICAL TOXICOLOGY

13.1 Carcinogenesis, Mutagenesis, Impairment of Fertility

[See Warnings and Precautions (5.2, 5.11)]

14 CLINICAL STUDIES

In an active-controlled clinical trial, 743 women 18 to 45 years of age were studied to assess the efficacy of norethindrone acetate and ethinyl estradiol tablets and ferrous fumarate tablets, for up to six 28-day cycles. The racial demographic of women randomized to norethindrone acetate and ethinyl estradiol tablets and ferrous fumarate tablets was: 69.5% Caucasian, 15.5% African-American, 10.4% Hispanic, 2.3% Asian and 2.3% Native American/Other. Women with body mass index (BMI) greater than 35 mg/m^2 were excluded from the study. The weight range for those women treated was 90 to 260 pounds, with a mean weight of 147 pounds. Among the women in the study randomized to norethindrone acetate and ethinyl estradiol tablets and ferrous fumarate tablets, 38.9% had not used hormonal contraception immediately prior to enrolling in this study.

A total of 583 women completed 6 cycles of treatment. There were a total of 5 on-treatment pregnancies among women aged 18 to 45 years in 3,565 treatment cycles during which no back-up contraception was used. The Pearl Index for norethindrone acetate and ethinyl estradiol tablets and ferrous fumarate tablets was 1.82 (95% confidence interval 0.59 to 4.25).

16 HOW SUPPLIED/STORAGE AND HANDLING

16.1 How Supplied

Hailey® 24 Fe (norethindrone acetate and ethinyl estradiol tablets, USP and ferrous fumarate tablets, USP) is available in cartons (NDC 68462-731-29) of three blisters (NDC 68462-731-84).

Each blister (28 tablets) contains in the following order:

- 24 white to off-white, round, flat faced beveled edge, uncoated tablets debossed with ‘16’ on one side and ‘G’ on the other side and each containing 1 mg norethindrone acetate, USP and 20 mcg ethinyl estradiol, USP.
- 4 brown to dark brown, round, flat faced beveled edge, uncoated tablets debossed with ‘17’ on one side and ‘G’ on the other side and each containing 75 mg ferrous fumarate, USP. The ferrous fumarate tablets do not serve any therapeutic purpose.

16.2 Storage Conditions

- Store at 20ºC to 25ºC (68ºF to 77ºF); excursions permitted from 15ºC to 30ºC (59ºF to 86ºF) [see USP Controlled Room Temperature].
- Protect from light.

17 PATIENT COUNSELING INFORMATION

Counsel patients to read the FDA-approved Patient Labeling (Patient Information and Instructions for Use).

Counsel patients about the following information:

- Cigarette smoking increases the risk of serious cardiovascular events from COC use, and that women who are over 35 years old and smoke should not use COCs [see Boxed Warning].
- Increased risk of VTE compared to non-users of COCs is greatest after initially starting a COC or restarting (following a 4-week or greater pill-free interval) the same or a different COC [see Warnings and Precautions (5.1)].
- Hailey 24 Fe does not protect against HIV infection (AIDS) and other sexually transmitted diseases.
- Hailey 24 Fe is not to be used during pregnancy; if pregnancy occurs during use of Hailey 24 Fe instruct the patient to stop further use [see Warnings and Precautions (5.9)].
- Take one tablet daily by mouth at the same time every day. Instruct patients what to do in the event pills are missed [see Dosage and Administration (2.2)].
- Use a back-up or alternative method of contraception when enzyme inducers are used with Hailey 24 Fe [see Drug Interactions (7.1)].
- COCs may reduce breast milk production; this is less likely to occur if breastfeeding is well established [see Use in Specific Populations (8.2)].
- Women who start COCs postpartum, and who has not yet had a period, must use an additional method of contraception until she has taken a white to off-white tablet for 7 consecutive days [see Dosage and Administration (2.2)].
- Amenorrhea may occur. Consider pregnancy in the event of amenorrhea at the time of the first missed period. Rule out pregnancy in the event of amenorrhea in two or more consecutive cycles [see Warnings and Precautions (5.8)].

Distributed by:

Glenmark Pharmaceuticals Inc., USA

Elmwood Park, NJ 07407

Questions? 1 (888) 721-7115

www.glenmarkpharma-us.com

May 2025

PATIENT INFORMATION

Hailey® 24 Fe (HAY-lee 24 Fe)
(norethindrone acetate and ethinyl estradiol tablets, USP and ferrous fumarate tablets, USP)

What is the most important information I should know about Hailey 24 Fe?

Do not use Hailey 24 Fe if you smoke cigarettes and are over 35 years old. Smoking increases your risk of serious cardiovascular side effects from hormonal birth control pills, including death from heart attack, blood clots or stroke. This risk increases with age and the number of cigarettes you smoke.

What is Hailey 24 Fe?

Hailey 24 Fe is a birth control pill (hormonal contraceptive) used by women to prevent pregnancy.

How does Hailey 24 Fe work for contraception?

Your chance of getting pregnant depends on how well you follow the directions for taking your birth control pills. The better you follow the directions, the less chance you have of getting pregnant.

Based on the results from the clinical study, about 1 to 4 out of 100 women may get pregnant during the first year they use Hailey 24 Fe.

The following chart shows the chance of getting pregnant for women who use different methods of birth control. Each box on the chart contains a list of birth control methods that are similar in effectiveness. The most effective methods are at the top of the chart. The box on the bottom of the chart shows the chance of getting pregnant for women who do not use birth control and are trying to get pregnant.

Who should not take Hailey 24 Fe?

Do not take Hailey 24 Fe if you:

- smoke and are over 35 years of age
- had blood clots in your arms, legs, lungs, or eyes
- had a problem with your blood that makes it clot more than normal
- have certain heart valve problems or irregular heart beat that increases your risk of having blood clots
- had a stroke
- had a heart attack
- have high blood pressure that cannot be controlled by medicine
- have diabetes with kidney, eye, nerve, or blood vessel damage
- have certain kinds of severe migraine headaches with aura, numbness, weakness or changes in vision, or any migraine headaches if you are over 35 years of age
- have liver problems, including liver tumors
- have any unexplained vaginal bleeding
- had breast cancer
- take any Hepatitis C drug combination containing ombitasvir/paritaprevir/ritonavir, with or without dasabuvir. This may increase levels of the liver enzyme “alanine aminotransferase” (ALT) in the blood.

If any of these conditions happen while you are taking Hailey 24 Fe, stop taking Hailey 24 Fe right away and talk to your healthcare provider. Use non-hormonal contraception (such as condoms and spermicide) when you stop taking Hailey 24 Fe.

What should I tell my healthcare provider before taking Hailey 24 Fe?

Tell your healthcare provider if you:

- are pregnant or think you may be pregnant
- are depressed now or have been depressed in the past
- had yellowing of your skin or eyes (jaundice) caused by pregnancy (cholestasis of pregnancy)
- are breastfeeding or plan to breastfeed. Hailey 24 Fe may decrease the amount of breast milk you make. A small amount of the hormones in Hailey 24 Fe may pass into your breast milk. Talk to your healthcare provider about the best birth control method for you while breastfeeding.

Tell your healthcare provider about all the medicines you take, including prescription and over-the-counter medicines, vitamins and herbal supplements.

Hailey 24 Fe may affect the way other medicines work, and other medicines may affect how well Hailey 24 Fe works.

Know the medicines you take. Keep a list of them to show your healthcare provider and pharmacist when you get a new medicine.

How should I take Hailey 24 Fe?

Read the Instructions for Use at the end of this Patient Information.

What are the possible serious side effects of Hailey 24 Fe?

- Like pregnancy, Hailey 24 Fe may cause serious side effects, including blood clots in your lungs, heart attack, or a stroke that may lead to death. Some other examples of serious blood clots include blood clots in the legs or eyes.

Serious blood clots can happen especially if you smoke, are obese, or are older than 35 years of age. Serious blood clots are more likely to happen when you:

- first start taking birth control pills
- restart the same or different birth control pills after not using them for a month or more

Call your healthcare provider or go to a hospital emergency room right away if you have:

- leg pain that will not go away

- a sudden, severe headache unlike your usual headaches

- sudden severe shortness of breath

- weakness or numbness in your arm or leg

- sudden change in vision or blindness

- trouble speaking

- chest pain

Other serious side effects include:

- liver problems, including:
  - rare liver tumors
  - jaundice (cholestasis), especially if you previously had cholestasis of pregnancy. Call your healthcare provider if you have yellowing of your skin or eyes.
- high blood pressure. You should see your healthcare provider for a yearly check of your blood pressure.
- gallbladder problems
- changes in the sugar and fat (cholesterol and triglycerides) levels in your blood
- new or worsening headaches including migraine headaches
- depression
- possible cancer in your breast and cervix
- swelling of your skin especially around your mouth, eyes, and in your throat (angioedema). Call your healthcare provider if you have a swollen face, lips, mouth tongue or throat, which may lead to difficulty swallowing or breathing. Your chance of having angioedema is higher is you have a history of angioedema.
- dark patches of skin around your forehead, nose, cheeks and around your mouth, especially during pregnancy (chloasma). Women who tend to get chloasma should avoid spending a long time in sunlight, tanning booths, and under sun lamps while taking Hailey 24 Fe. Use sunscreen if you have to be in the sunlight.

What are the most common side effects of Hailey 24 Fe?

- headache
- vaginal infections
- nausea
- menstrual cramps
- breast tenderness
- mood changes
- acne
- weight gain

These are not all the possible side effects of Hailey 24 Fe. For more information, ask your healthcare provider or pharmacist.

You may report side effects to the FDA at 1-800-FDA-1088.

What else should I know about taking Hailey 24 Fe?

- If you are scheduled for any lab tests, tell your healthcare provider you are taking Hailey 24 Fe. Certain blood tests may be affected by Hailey 24 Fe.
- Hailey 24 Fe does not protect against HIV infection (AIDS) and other sexually transmitted infections.

How should I store Hailey 24 Fe?

- Store Hailey 24 Fe at room temperature between 68°F to 77°F (20°C to 25°C).
- Store away from light.
- Keep Hailey 24 Fe and all medicines out of the reach of children.

General information about the safe and effective use of Hailey 24 Fe.

Medicines are sometimes prescribed for purposes other than those listed in a Patient Information leaflet. Do not use Hailey 24 Fe for a condition for which it was not prescribed. Do not give Hailey 24 Fe to other people.

This Patient Information summarizes the most important information about Hailey 24 Fe. You can ask your pharmacist or healthcare provider for information about Hailey 24 Fe that is written for health professionals.

For more information, call Glenmark Pharmaceuticals Inc., USA at 1 (888) 721-7115.

Do birth control pills cause cancer?

It is not known if hormonal birth control pills cause breast cancer. Some studies, but not all, suggest that there could be a slight increase in the risk of breast cancer among current users with longer duration of use.

If you have breast cancer now, or have had it in the past, do not use hormonal birth control because some breast cancers are sensitive to hormones.

Women who use birth control pills may have a slightly higher chance of getting cervical cancer. However, this may be due to other reasons such as having more sexual partners.

What if I want to become pregnant?

You may stop taking the pill whenever you wish. Consider a visit with your healthcare provider for a pre-pregnancy checkup before you stop taking the pill.

What should I know about my period when taking Hailey 24 Fe?

Your periods may be lighter and shorter than usual. Some women may miss a period. Irregular vaginal bleeding or spotting may happen while you are taking Hailey 24 Fe, especially during the first few months of use. This usually is not a serious problem. It is important to continue taking your pills on a regular schedule to prevent a pregnancy.

What are the ingredients in Hailey 24 Fe?

Active ingredients:

White to off-white pills: norethindrone acetate and ethinyl estradiol

Inactive ingredients:

Brown to dark brown pills: ferrous fumarate

INSTRUCTIONS FOR USE

Hailey® 24 Fe (HAY-lee 24 Fe)
(norethindrone acetate and ethinyl estradiol tablets and ferrous fumarate tablets)

Important Information about taking Hailey 24 Fe

- Take 1 pill every day at the same time. Take the pills in the order directed on your pill dispenser.
- Do not skip your pills, even if you do not have sex often. If you miss pills (including starting the pack late), you could get pregnant. The more pills you miss, the more likely you are to get pregnant.
- If you have trouble remembering to take Hailey 24 Fe, talk to your healthcare provider.
- When you first start taking Hailey 24 Fe, spotting or light bleeding in between your periods may occur. Contact your healthcare provider if this does not go away after a few months.
- You may feel sick to your stomach (nauseous), especially during the first few months of taking Hailey 24 Fe. If you feel sick to your stomach, do not stop taking the pill. The problem will usually go away. If your nausea does not go away, call your healthcare provider.
- Missing pills can also cause spotting or light bleeding, even when you take the missed pills later. On the days you take 2 pills to make up for missed pills (see, What should I do if I miss any Hailey 24 Fe pills? below), you could also feel a little sick to your stomach.
- It is not uncommon to miss a period. However, if you miss a period and have not taken Hailey 24 Fe according to directions, or miss 2 periods in a row, or feel like you may be pregnant, call your healthcare provider. If you have a positive pregnancy test, you should stop taking Hailey 24 Fe.
- If you have vomiting or diarrhea within 3 to 4 hours of taking a white to off-white active pill, take another white to off-white pill from your extra pill dispenser. If you do not have an extra pill dispenser, take the next white to off-white pill in your pill dispenser. Continue taking all your remaining pills in order. Start the first pill of your next pill dispenser the day after finishing your current pill dispenser. This will be 1 day earlier than originally scheduled. Continue on your new schedule.
- If you have vomiting or diarrhea for more than 1 day, your birth control pills may not work as well. Use an additional birth control method, like condoms and a spermicide, until you check with your healthcare provider.
- Stop taking Hailey 24 Fe at least 4 weeks before you have major surgery and do not restart after the surgery without asking your healthcare provider. Be sure to use other forms of contraception (like condoms and spermicide) during this time period.

Before you start taking Hailey 24 Fe:

- Decide what time of day you want to take your pill. It is important to take it at the same time every day and in the order as directed on your pill dispenser.
- Have backup contraception (condoms and spermicide) available and if possible, an extra full pack of pills as needed.

When should I start taking Hailey 24 Fe?

If you start taking Hailey 24 Fe and you have not used a hormonal birth control method before:

- There are 2 ways to start taking your birth control pills. You can either start on a Sunday (Sunday Start) or on the first day (Day 1) of your natural menstrual period (Day 1 Start). Your healthcare provider should tell you when to start taking your birth control pill.
- If you use the Sunday Start, use non-hormonal back-up contraception such as condoms and spermicide for the first 7 days that you take Hailey 24 Fe. You do not need back-up contraception if you use the Day 1 Start.

If you start taking Hailey 24 Fe and you are switching from another birth control pill:

- Start your new Hailey 24 Fe pack on the same day that you would start the next pack of your previous birth control method.
- Do not continue taking the pills from your previous birth control pack.

If you start taking Hailey 24 Fe and previously used a vaginal ring or transdermal patch:

- Start using Hailey 24 Fe on the day you would have reapplied the next ring or patch.

If you start taking Hailey 24 Fe and you are switching from a progestin-only method such as an implant or injection:

- Start taking Hailey 24 Fe on the day of removal of your implant or on the day when you would have had your next injection.

If you start taking Hailey 24 Fe and you are switching from an intrauterine device or system (IUD or IUS):

- Start taking Hailey 24 Fe on the day of removal of your IUD or IUS.
- You do not need back-up contraception if your IUD or IUS is removed on the first day (Day 1) of your period. If your IUD or IUS is removed on any other day, use non-hormonal back-up contraception such as condoms and spermicide for the first 7 days that you take Hailey 24 Fe.

Keep a calendar to track your period:

If this is the first time you are taking birth control pills, read, “When should I start taking Hailey 24 Fe?” above. Follow these instructions for either a Sunday Start or a Day 1 Start.

Sunday Start:

You will use a Sunday Start if your healthcare provider told you to take your first pill on a Sunday.

- Take pill 1 on the Sunday after your period starts.
- If your period starts on a Sunday, take pill “1” that day and refer to Day 1 Start instructions below.
- Take 1 pill every day in the order on the pill dispenser at the same time each day for 28 days.
- After taking the last pill on Day 28 from the pill dispenser, start taking the first pill from a new pack, on the same day of the week as the first pack (Sunday). Take the first pill in the new pack whether or not you are having your period.
- Use non-hormonal back-up contraception such as condoms and spermicide for the first 7 days of the first cycle that you take Hailey 24 Fe.

Day 1 Start:

You will use a Day 1 Start if your doctor told you to take your first pill (Day 1) on the first day of your period.

- Take 1 pill every day in the order of the pill dispenser dial pack, at the same time each day, for 28 days.
- After taking the last pill on Day 28 from the pill dispenser, start taking the first pill from a new pack, on the same day of the week as the first pack. Take the first pill in the new pack whether or not you are having your period.

Instructions for using your pill pack:

The Hailey 24 Fe pill pack has 24 "active" white to off-white pills (with hormones) to be taken for 24 days, followed by 4 "reminder" brown to dark brown pills (without hormones) to be taken for the next 4 days.

Look for:

- Where on the pack to start taking pills
- In what order to take the pills. Follow the arrows shown in Figure A.
- The week numbers as shown in Figure A.

What if should I do if I miss any Hailey 24 Fe white to off-white pills?

If you miss 1 white to off-white pill in Weeks 1, 2, or 3, follow these steps:

- Take it as soon as you remember. Take the next pill at your regular time. This means you may take 2 pills in 1 day.
- Then continue taking 1 pill every day until you finish the pack.
- You do not need to use a back-up birth control method if you have sex.

If you miss 2 white to off-white pills in a row in Week 1 or Week 2 of your pack, follow these steps:

- Take the 2 missed pills as soon as possible and the next 2 pills the next day.
- Then continue to take 1 pill every day until you finish the pack.
- Use a non-hormonal birth control method (such as a condom and spermicide) as a back-up if you have sex during the first 7 days after missing your pills.

If you miss 2 white to off-white pills in a row in Week 3 or Week 4, or you miss 3 or more white to off-white pills in a row at any time, follow these steps:

- If you are a Day 1 Starter:
  - Throw out the rest of the pill pack and start a new pack that same day.
- If you are a Sunday Starter:
  - Keep taking 1 pill every day until Sunday. On Sunday, throw out the rest of the pack and start a new pack of pills that same day.
- You may not have your period this month but this is expected. However, if you miss your period 2 months in a row, call your healthcare provider because you might be pregnant.
- You could become pregnant if you have sex during the first 7 days after you restart your pills. You MUST use a non-hormonal birth control method (such as a condom and spermicide) as a back-up if you have sex during the first 7 days after you restart your pills.

If you miss any of the 4 brown to dark brown “reminder” pills in Week 4, throw away the pills you missed and keep taking 1 pill each day until the pack is empty. You do not need to use a back-up method of birth control.

If you have any questions or are unsure about the information in this leaflet, call your healthcare provider.

This Patient Information and Instructions for Use has been approved by the U.S. Food and Drug Administration.

Distributed by:

Glenmark Pharmaceuticals Inc., USA

Elmwood Park, NJ 07407

Questions? 1 (888) 721-7115

www.glenmarkpharma-us.com

May 2025